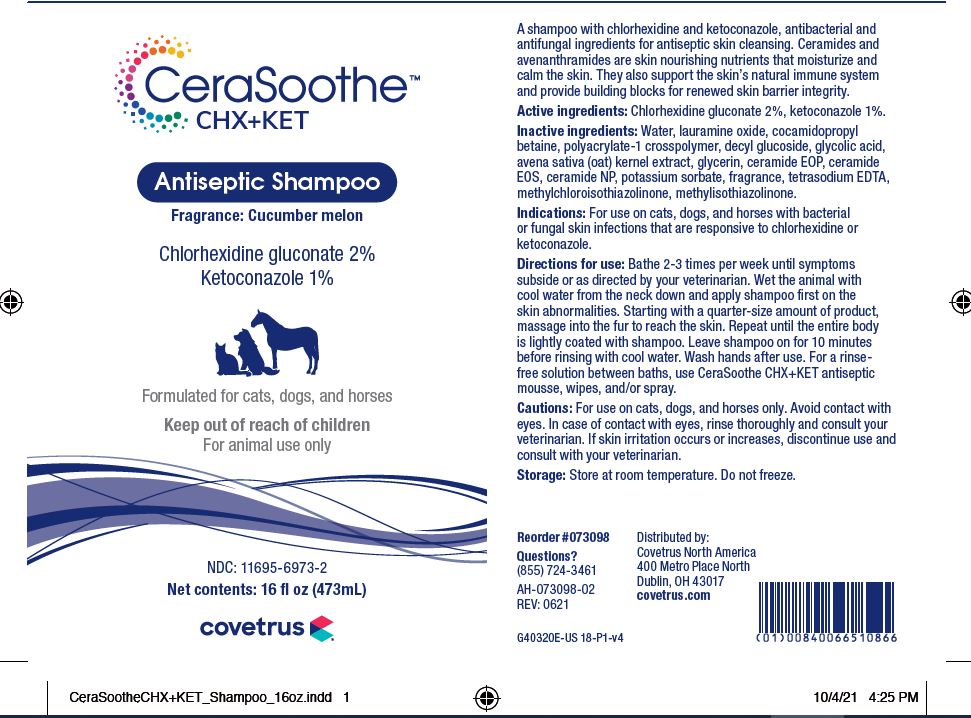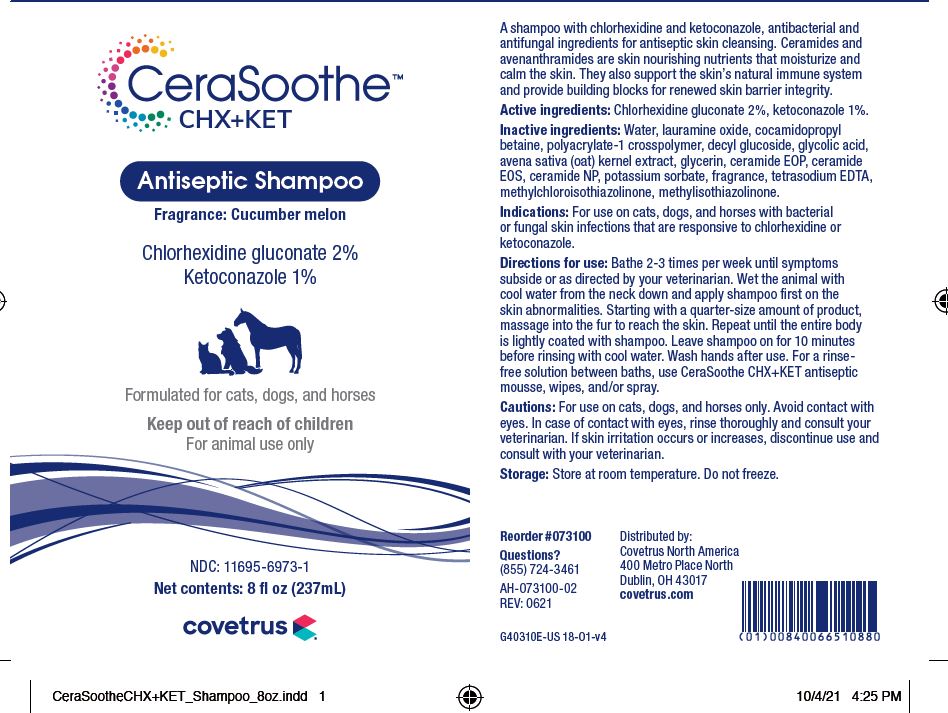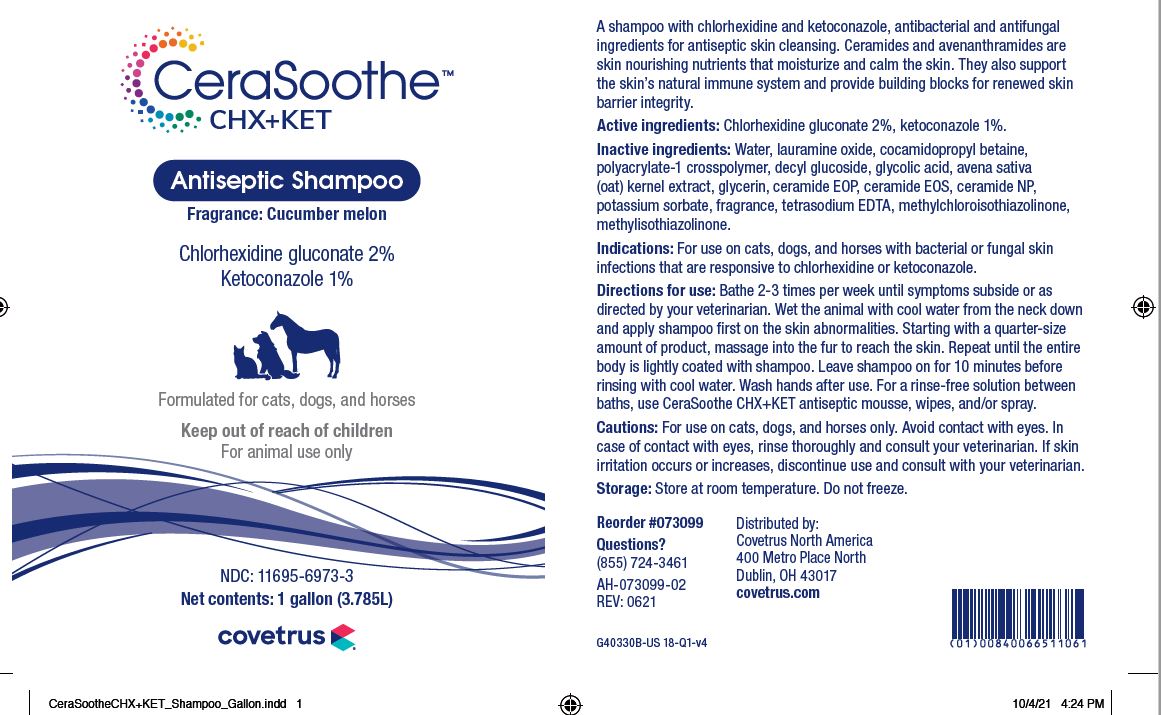 DRUG LABEL: CeraSoothe
NDC: 11695-6973 | Form: SHAMPOO
Manufacturer: BUTLER ANIMAL HEALTH SUPPLY, LLC DBA COVETRUS NORTH AMERICA
Category: animal | Type: OTC ANIMAL DRUG LABEL
Date: 20220412

ACTIVE INGREDIENTS: CHLORHEXIDINE GLUCONATE 20 mg/1 mL; KETOCONAZOLE 10 mg/1 mL
INACTIVE INGREDIENTS: WATER; LAURAMINE OXIDE; COCAMIDOPROPYL BETAINE; CARBOMER HOMOPOLYMER, UNSPECIFIED TYPE; DECYL GLUCOSIDE; GLYCOLIC ACID; AVENANTHRAMIDES; GLYCERIN; CERAMIDE 1; CERAMIDE EOS; CERAMIDE NP; POTASSIUM SORBATE; EDETATE SODIUM; METHYLCHLOROISOTHIAZOLINONE; METHYLISOTHIAZOLINONE

DESCRIPTION

CeraSoothe CHX+KET

Antiseptic Shampoo

Fragrance: Cucumber melon

Formulated for cats, dogs and horses

Keep out of reach of children

For animal use only

A shampoo with chlorhexidine and ketoconazole, antibacterial and antifungal ingredients for antiseptic skin cleansing. Ceramides and avenanthramides are skin nourishing nutrients that moisturize and calm the skin. They also support the skin’s natural immune system and provide building blocks for renewed skin barrier integrity.

Active ingredients: Chlorhexidine gluconate 2%, ketoconazole 1%.

Inactive ingredients: Water, lauramine oxide, cocamidopropyl betaine, polyacrylate-1 crosspolymer, decyl glucoside, glycolic acid, avena sativa (oat) kernel extract, glycerin, ceramide EOP, ceramide EOS, ceramide NP, potassium sorbate, fragrance, tetrasodium EDTA, methylchloroisothiazolinone, methylisothiazolinone.

INDICATIONS AND USAGE

Indications: For use on cats, dogs, and horses with bacterial or fungal skin infections that are responsive to chlorhexidine gluconate and ketoconazole.

Directions for use: Bathe 2-3 times per week until symptoms subside or as directed by your veterinarian. Wet the animal with cool water from the neck down and apply shampoo first on the skin abnormalities. Starting with a quarter-size amount of product, massage into the fur to reach the skin. Repeat until the entire body is lightly coated with shampoo. Leave shampoo on for 10 minutes before rinsing with cool water. Wash hands after use. For a rinse-free solution between baths, use CeraSoothe CHX+KET antiseptic mousse, wipes, and/or spray.

WARNINGS AND PRECAUTIONS

Cautions: For use on cats, dogs and horses only. Avoid contact with eyes. In case of contact with eyes, rinse thoroughly and consult your veterinarian. If skin irritation occurs or increases, discontinue use and consult your veterinarian.

Storage: Store at room temperature. Do not freeze.

QUESTIONS?

(855) 724-3461

Distributed by:

Covetrus North America

400 Metro Place North

Dublin, OH 43017

covetrus.com

PRINCIPAL DISPLAY PANEL - 8 OUNCE (237 mL) Bottle

Inspired by veterinarians

CeraSoothe CHX+KET

Antiseptic Shampoo

Fragrance: Cucumber melon

Chlorhexidine gluconate 2%

Ketoconazole 1%

Formulated for cats, dogs and horses

Keep out of reach of children

For animal use only

NDC: 11695-6973-1

Net contents: 8 fl oz (237 mL)

PRINCIPAL DISPLAY PANEL - 16 OUNCE (473 mL) Bottle

Inspired by veterinarians

CeraSoothe CHX+KET

Antiseptic Shampoo

Fragrance: Cucumber melon

Chlorhexidine gluconate 2%

Ketoconazole 1%

Formulated for cats, dogs and horses

Keep out of reach of children

For animal use only

NDC: 11695-6973-2

Net contents: 16 fl oz (473 mL)

PRINCIPAL DISPLAY PANEL - 1 Gallon (3.785L) Jug

Inspired by veterinarians

CeraSoothe CHX+KET

Antiseptic Shampoo

Fragrance: Cucumber melon

Chlorhexidine gluconate 2%

Ketoconazole 1%

Formulated for cats, dogs and horses

Keep out of reach of children

For animal use only

NDC: 11695-6973-3

Net contents: 1 gallon (3.785L)